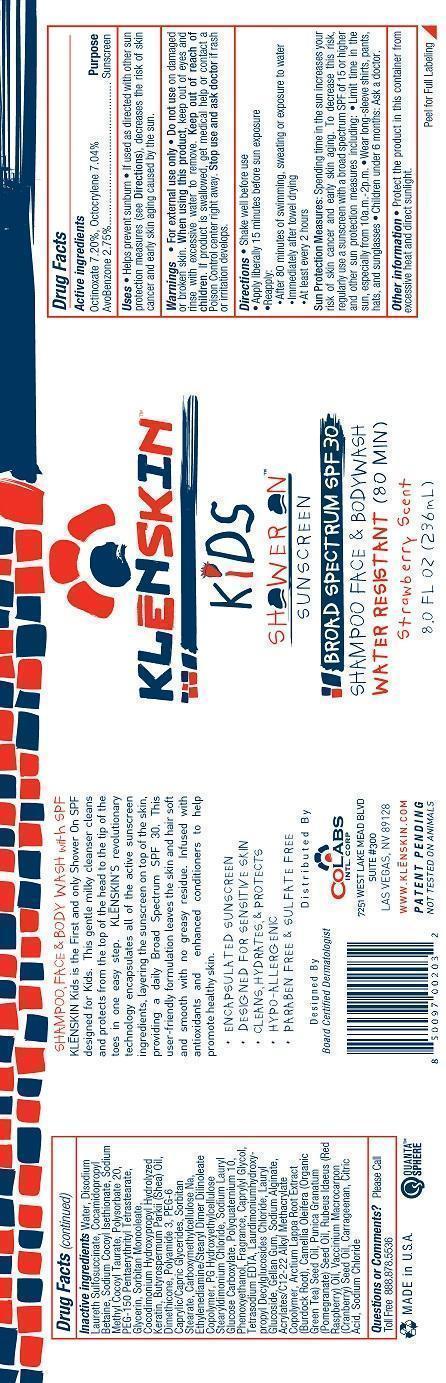 DRUG LABEL: KLENSKIN KIDS SHOWERON SUNSCREEN
NDC: 61369-102 | Form: GEL
Manufacturer: CoLabs Intl. Corp
Category: otc | Type: HUMAN OTC DRUG LABEL
Date: 20240115

ACTIVE INGREDIENTS: AVOBENZONE 2.75 g/100 mL; OCTOCRYLENE 7.04 g/100 mL; OCTINOXATE 7.2 g/100 mL
INACTIVE INGREDIENTS: WATER; LAURYL SULFOSUCCINATE; COCAMIDOPROPYL BETAINE; SODIUM COCOYL ISETHIONATE; SODIUM METHYL COCOYL TAURATE; POLYSORBATE 20; PEG-150 PENTAERYTHRITYL TETRASTEARATE; GLYCERIN; SORBITAN MONOOLEATE; HYDROLYZED ELASTIN, BOVINE, ALKALINE (1000 MW); SHEANUT OIL; DIMETHICONE; POLYACRYLAMIDE (1500 MW); PEG-6 CAPRYLIC/CAPRIC GLYCERIDES; SORBITAN MONOSTEARATE; CARBOXYMETHYLCELLULOSE SODIUM, UNSPECIFIED FORM; ETHYLENEDIAMINE; DIISOSTEARYL DIMER DILINOLEATE; HYDROXYETHYL CELLULOSE (140 MPA.S AT 5%); SODIUM LAURYL GLYCOL CARBOXYLATE; POLYQUATERNIUM-10 (1000 MPA.S AT 2%); PHENOXYETHANOL; CAPRYLYL GLYCOL; EDETATE SODIUM; DECYL GLUCOSIDE; LAURYL GLUCOSIDE; GELLAN GUM (LOW ACYL); SODIUM ALGINATE; CARBOMER COPOLYMER TYPE A; ARCTIUM LAPPA ROOT; GREEN TEA LEAF; POMEGRANATE; RASPBERRY SEED OIL; CRANBERRY SEED OIL; CARRAGEENAN; ANHYDROUS CITRIC ACID; SODIUM CHLORIDE

COLABS - KLENSKIN KIDS SHOWERON SUNSCREEN SPF 30(61369-102)

ACTIVE INGREDIENTS

AVOBENZONE 2.75%

OCTOCRYLENE 7.04%

OCTINOXATE 7.2%

PURPOSE

SUNSCREEN

USES

- HELPS PREVENT SUNBURN
- IF USED AS DIRECTED WITH OTHER SUN PROTECTION MEASURES (SEE DIRECTIONS), DECREASES THE RISK OF SKIN CANCER AND EARLY SKIN AGING CAUSED BY THE SUN.

WARNINGS

- FOR EXTERNAL USE ONLY
- DO NOT USE ON DAMAGED OR BROKEN SKIN.
- WHEN USING THIS PRODUCT, KEEP OUT OF EYES AND RINSE WITH EXCESSIVE WATER TO REMOVE.

KEEP OUT OF REACH OF CHILDREN. IF PRODUCT IS SWALLOWED, GET MEDICAL HELP OR CONTACT A POISON CONTROL CENTER RIGHT AWAY.

STOP USE AND ASK A DOCTOR IF RASH OR IRRITATION DEVELOPS.

DIRECTIONS

- SHAKE WELL BEFORE USE
- APPLY LIBERALLY 15 MINUTES BEFORE SUN EXPOSURE
- REAPPLY:
- AFTER 80 MINUTES OF SWIMMING, SWEATING OR EXPOSURE TO WATER
- IMMEDIATELY AFTER TOWEL DRYING
- AT LEAST EVERY 2 HOURS

OTHER SAFETY INFORMATION

SUN PROTECTION MEASURES: SPENDING TIME IN THE SUN INCREASES YOUR RISK OF SKIN CANCER AND EARLY SKIN AGING. TO DECREASE THIS RISK, REGULARLY USE A SUNSCREEN WITH A BROAD SPECTRUM SPF OF 15 OR HIGHER AND OTHER SUN PROTECTION MEASURES INCLUDING:

- LIMIT TIME IN THE SUN, ESPECIALLY FROM 10 A.M. - 2 P.M.
- WEAR LONG-SLEEVED SHIRTS, PANTS, HATS, AND SUNGLASSES
- CHILDREN UNDER 6 MONTHS: ASK A DOCTOR.

OTHER INFORMATION

- PROTECT THE PRODUCT IN THIS CONTAINER FROM EXCESSIVE HEAT AND DIRECT SUNLIGHT.

INACTIVE INGREDIENTS

WATER, DISODIUM LAURETH SULFOSUCCINATE, COCAMIDOPROPYL BETAINE, SODIUM COCOYL ISETHIONATE, SODIUM METHYL COCOYL TAURATE, POLYSORBATE 20, PEG-150 PENTAERYTHRITYL TETRASTEARATE, GLYCERIN, SORBITAN MONOOLEATE, COCODIMONIUM HYDROXYPROPYL HYDROLYZED KERATIN, BUTYROSPERMUM PARKII (SHEA) OIL, DIMETHICONE, POLYAMIDE-3, PEG-6 CAPRYLIC/CAPRIC GLYCERIDES, SORBITAN STEARATE, CARBOXYMETHYCELLULOSE NA, ETHYLENEDIAMNE/STEARYL DIMER DILINOLEATE COPOLYMER, PG HYDROXYETHYLCELLULOSE STEARYLDIMONIUM CHLORIDE, SODIUM LAURYL GLUCOSE CARBOXYLATE, POLYQUATERNIUM 10, PHENOXYETHANOL, FRAGRANCE, CAPRYLYL GLYCOL, TETRASODIUM EDTA, LAURDIMONIUMHYDROXYPROPYL DECYLGLUCOSIDES CHLORIDE, LAURYL GLUCOSIDE, GELLAN GUM, SODIUM ALGINATE, ACRYLATES/C12-22 ALKYL METHACRYLATE COPOLYMER, ARCTIUM LAPPA (BURDOCK ROOT) EXTRACT, CAMELIA OLEIFERA (GREEN TEA) SEED OIL, PUNICA GRANATUM (POMEGRANATE) SEED OIL, RUBEUS IDAEUS (RED RASPBERRY) OIL, VACCINIUM MACROCARPON (CRANBERRY) SEED OIL, CARRAGEENAN, CITRIC ACID, SODIUM CHLORIDE

QUESTIONS OR COMMENTS? PLEASE CALL TOLL FREE 888.878.5536